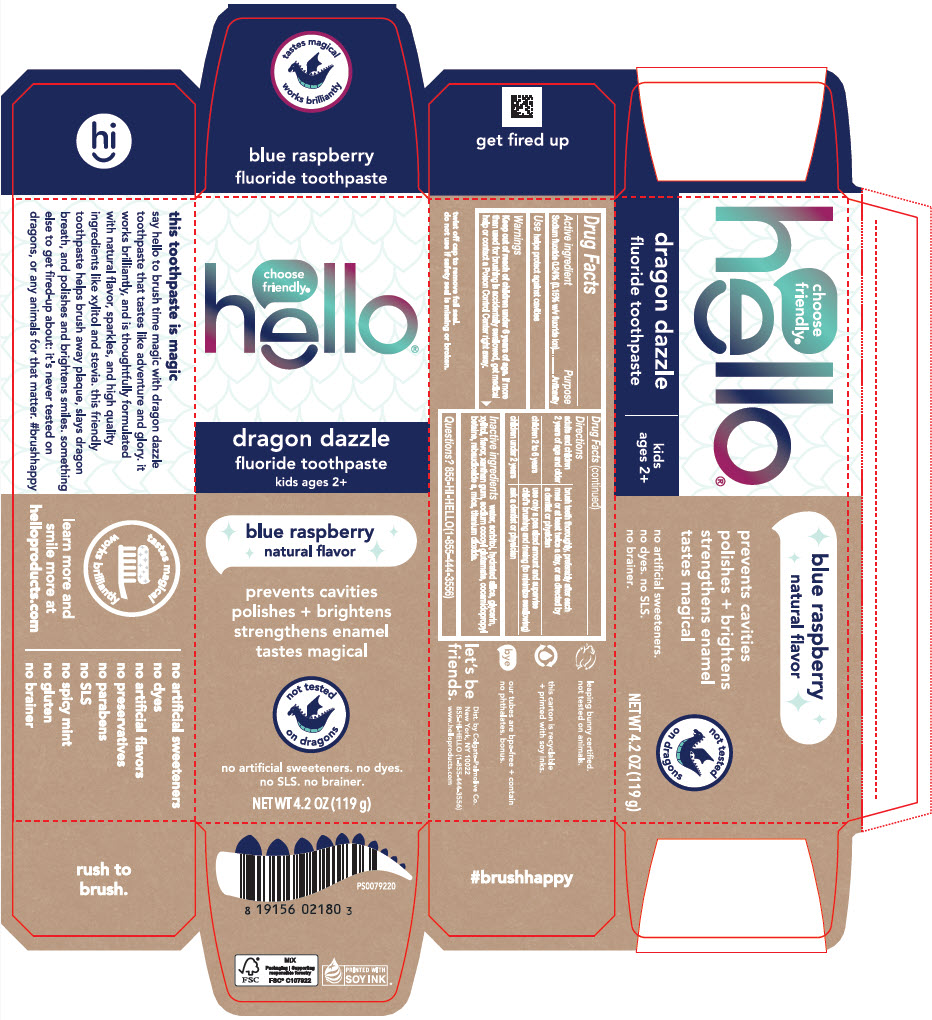 DRUG LABEL: Hello Dragon Dazzle 
NDC: 35000-679 | Form: PASTE, DENTIFRICE
Manufacturer: Colgate-Palmolive Company
Category: otc | Type: HUMAN OTC DRUG LABEL
Date: 20250528

ACTIVE INGREDIENTS: SODIUM FLUORIDE 1.5 mg/1 g
INACTIVE INGREDIENTS: SORBITOL; HYDRATED SILICA; WATER; XYLITOL; GLYCERIN; XANTHAN GUM; TITANIUM DIOXIDE; COCAMIDOPROPYL BETAINE; SODIUM COCOYL GLUTAMATE; STEVIA REBAUDIUNA LEAF; MICA

Hello® Dragon Dazzle
Dragon Dazzle Fluoride

Drug Facts

Active Ingredient

Sodium fluoride 0.24% (0.15% w/v fluoride ion).

Purpose

Anticavity

Use

helps protect against cavities

Warnings

Keep out of reach of children under 6 years of age.

If more than used for brushing is accidentally swallowed, get medical help or contact a Poison Control Center right away.

Directions

- adults and children 2 years of age and older: brush teeth thoroughly, preferably after each meal or at least twice a day, or as directed by a dentist or physician
- children 2 to 6 years: use only a pea sized amount and supervise child's brushing and rinsing (to minimize swallowing)
- children under 2 years: ask a dentist or a physician.

Inactive ingredients

sorbitol, purified water, hydrated silica, glycerin, xylitol, xanthan gum, flavor, cocamidopropyl betaine, sodium cocoyl glutamate, stevia rebaudiana leaf extract, mica and titanium dioxide.

Questions?

855-HI-HELLO (1-855-444-3556)

Dist. by Colgate-Palmolive Co.
New York, NY 10022

PRINCIPAL DISPLAY PANEL - 119 g Tube Carton

choose
friendly®
hello®

dragon dazzle
fluoride toothpaste
kids ages 2+

blue raspberry
natural flavor

prevents cavities
polishes + brightens
strengthens enamel
tastes magical

not tested
on dragons

no artificial sweeteners. no dyes.
no SLS. no brainer.

NET WT 4.2 OZ (119 g)